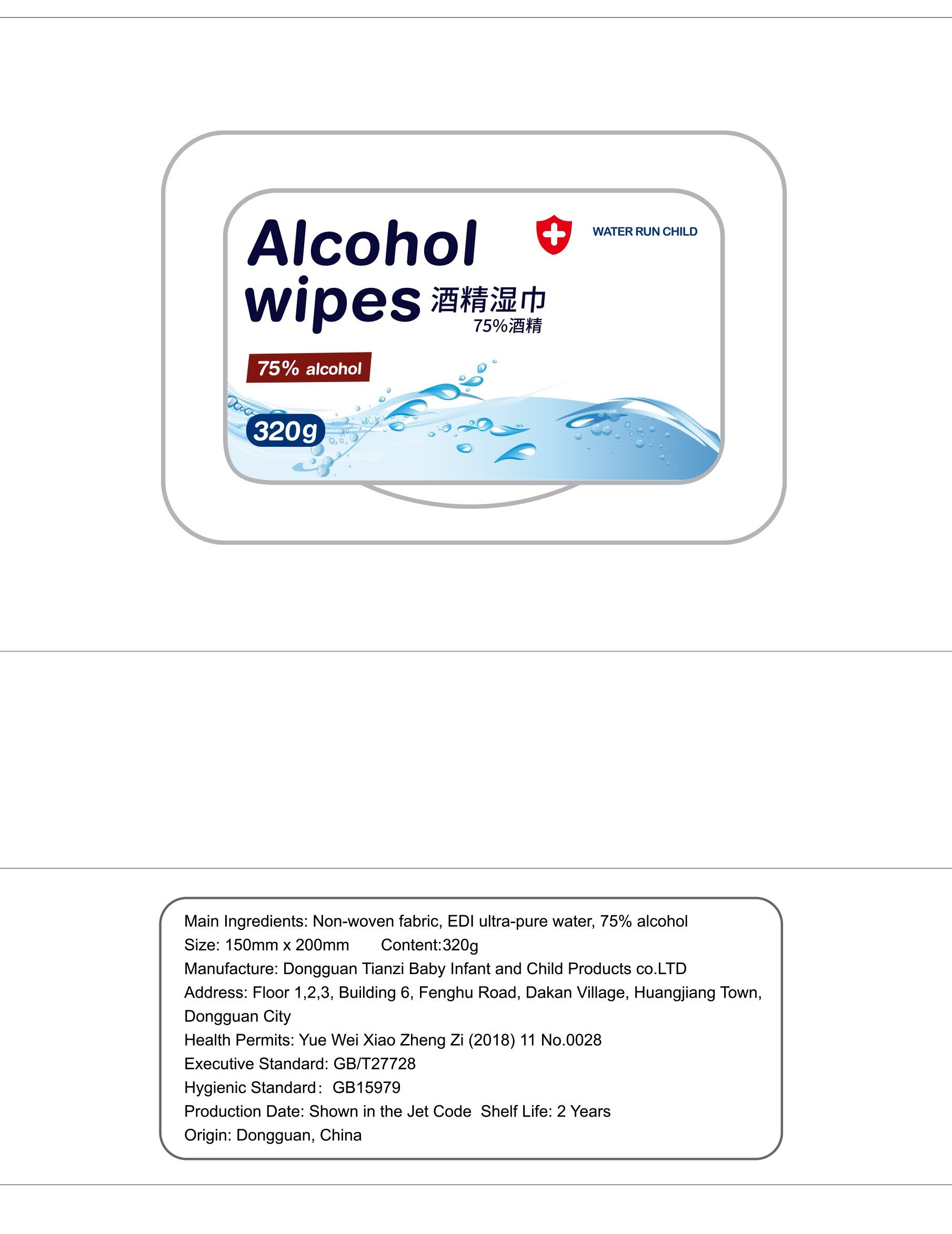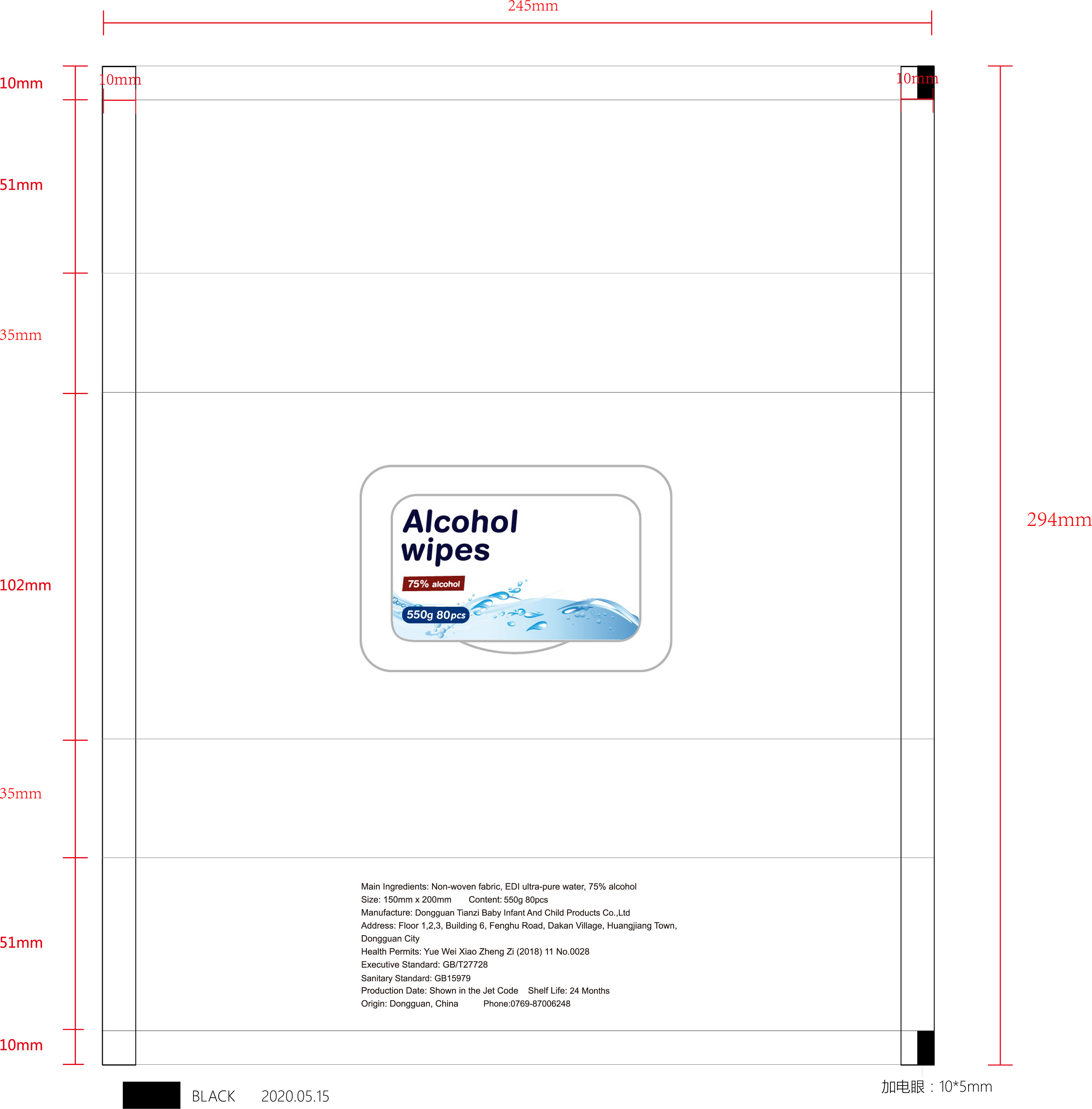 DRUG LABEL: Alcohol wipes
NDC: 75256-008 | Form: CLOTH
Manufacturer: Dongguan Tianzi Baby Infant And Child Products Co.,Ltd
Category: otc | Type: HUMAN OTC DRUG LABEL
Date: 20200520

ACTIVE INGREDIENTS: ALCOHOL 75 g/100 g
INACTIVE INGREDIENTS: WATER

Alochol wipes

Main Ingredients

75% alcohol

Purpose

Antiseptic

Inactive ingredients

EDI ultra-pure water